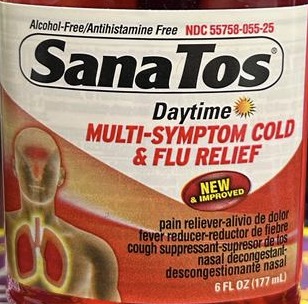 DRUG LABEL: Sanatos Multi Symptom Daytime
NDC: 55758-055 | Form: LIQUID
Manufacturer: Pharmadel LLC
Category: otc | Type: HUMAN OTC DRUG LABEL
Date: 20231117

ACTIVE INGREDIENTS: DEXTROMETHORPHAN HYDROBROMIDE 10 mg/15 mL; PHENYLEPHRINE HYDROCHLORIDE 5 mg/15 mL; ACETAMINOPHEN 325 mg/15 mL
INACTIVE INGREDIENTS: ANHYDROUS CITRIC ACID; WATER; FD&C YELLOW NO. 6; GLYCERIN; SUCROSE; PROPYLENE GLYCOL; SODIUM BENZOATE; SACCHARIN SODIUM

Sanatos Daytime MS 6 (APTA)

Active Ingredients & Purposes

PURPOSE

Active ingredients; (in each 15 mL, 1 tablespoon) | Purposes
Acetaminophen 325 mg | Pain reliever/fever reducer
Dextromethorphan HBr 10 mg | Cough suppressant
Phenylephrine HCI 5 mg | Nasal decongestant

Uses

temporarily relieves common cold/flu symptoms:

- minor aches & pains
- headache
- sore throat
- fever
- nasal congestion
- cough due to minor throat and bronchial irritation

Warnings

Liver warning: This product contains acetaminophen. Severe liver damage may occur if

- adults take more than 4,000 mg if acetaminophen in 24 hours
- child take more than 5 doses in 24 hours
- taken with other drugs containing acetaminophen
- adult has 3 or more alcoholic drinks every day while using this product

Allergy alert: Acetaminophen may cause severe skin reactions. Symptoms may include:

- Skin reddening
- Blisters
- Rash

If a skin reaction occurs, stop use and seek medical help right away.

Sore throat warning: If sore throat is severe, persists for more than 2 days, is accompanied or followed by fever, headache, rash, nausea, or vomiting, consult a doctor promptly.

Do not use

- if you are now taking a prescription monoamine oxidase inhibitor (MAOI) (certain drugs for depression, psychiatric or emotional conditions, or Parkinson's disease), or for 2 weeks after stopping the MAOI drug. If you do not know if your prescription drug contains an MAOI, ask a doctor or pharmacist before taking this product.
- with any other drug containing acetaminophen (prescription or nonprescription). If you are not sure whether a drug contains acetaminophen, ask a doctor or pharmacist.

Ask a doctor before use if you have

- liver disease
- heart disease
- thyroid disease
- diabetes
- high blood pressure
- trouble urinating due to enlarged prostate gland
- persistent or chronic cough such as occurs with smoking, asthma, or emphysema
- cough that occurs with too much phlegm (mucus)

When using this product

- do not use more than directed (see overdose warning)
- avoid alcoholic drinks

Stop use and ask a doctor if

- you get nervos, dizzy or sleepless
- new symptoms occur
- fever gets worse or lasts more than 3 days
- pain or cough gets worse or lasts more than 5 days (children) or 7 days (adults)
- redness or swelling is present
- cough comes back or occurs with rash or headache that lasts

These could be signs of a serious condition.

If pregnant or breast-feeding,

ask a health professional before use.

Overdose warning:

In case of overdose, get medical help or contact a Poison Control Center right away. Quick medical attention is critical for adults as well as for children even if you do not notice any signs or symptoms.

Directions

- take only as recommended (see overdose warning)
- use a dosage cup or tablespoon (TBSP)
- do not exceed 4 doses per 24 hrs

age | dose
adults & children 12 years & over | 30 mL (2 TBSP) every 4 hours
children 6 years to under 12 years | 15 mL (1 b TBSP) every 4 hours
children 4 years to under 6 years | ask a doctor
children under 4 years | do not use

- when using daytime and nighttime products, carefully read each label to ensure correct dosing.

Other information

- sodium content per tablespoon: 10 mg
- store at room temperature

TAMPER EVIDENT: Do not use if imprinted band is missing or broken.

Inactive ingredients

citric acid, FD&C yellow #6, flavor, glycerin, propylene glycol, purfied water, saccarhin sodium, sodium benzoate, sucrose

Questions?

call 1-866-359-3478

Distributed by:

Pharmadel LLC

Seaford, DE 19973

www.sanatos.com